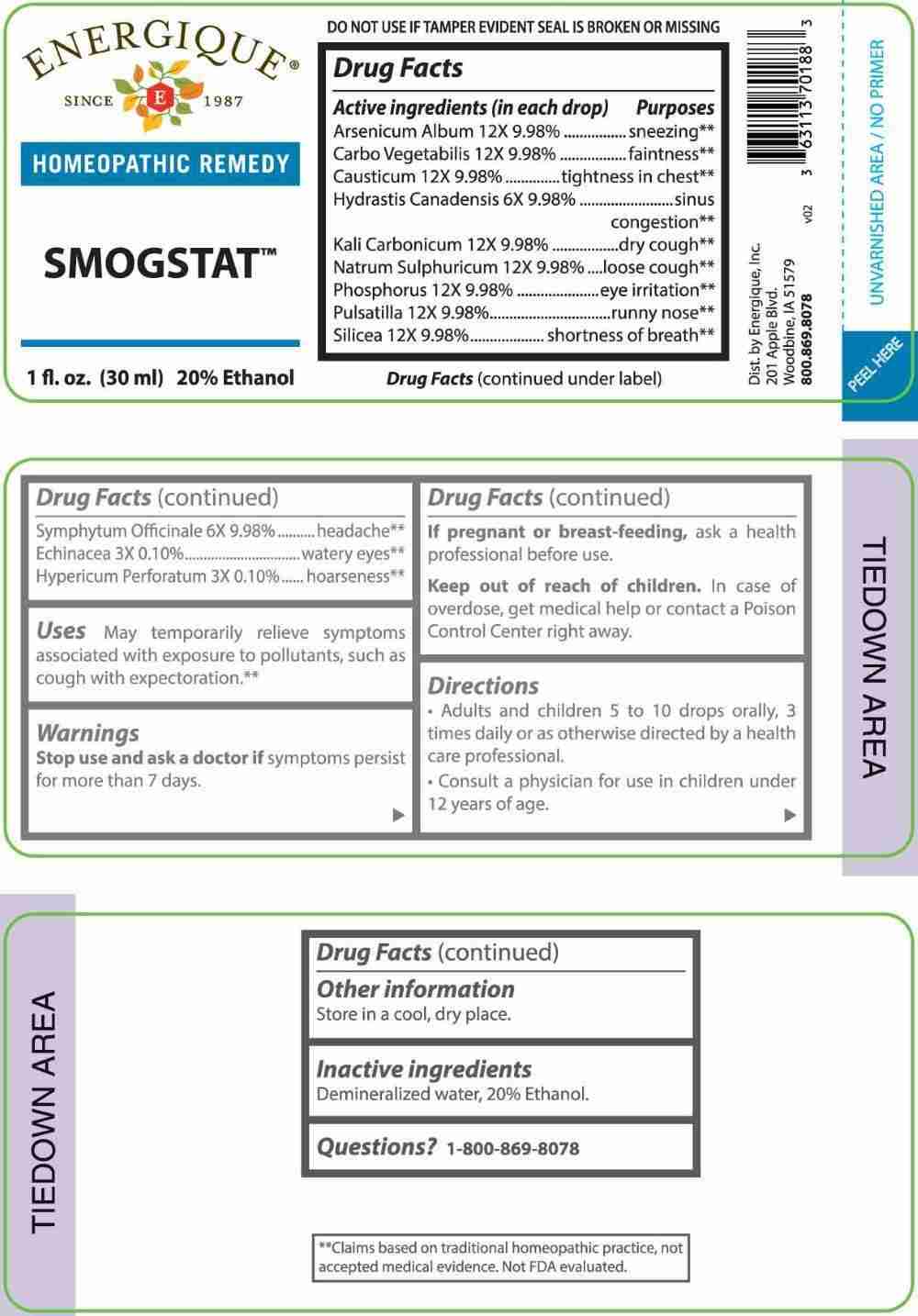 DRUG LABEL: Smogstat
NDC: 44911-0561 | Form: LIQUID
Manufacturer: Energique, Inc.
Category: homeopathic | Type: HUMAN OTC DRUG LABEL
Date: 20240725

ACTIVE INGREDIENTS: ECHINACEA ANGUSTIFOLIA WHOLE 3 [hp_X]/1 mL; HYPERICUM PERFORATUM WHOLE 3 [hp_X]/1 mL; GOLDENSEAL 6 [hp_X]/1 mL; COMFREY ROOT 6 [hp_X]/1 mL; ARSENIC TRIOXIDE 12 [hp_X]/1 mL; ACTIVATED CHARCOAL 12 [hp_X]/1 mL; CAUSTICUM 12 [hp_X]/1 mL; POTASSIUM CARBONATE 12 [hp_X]/1 mL; SODIUM SULFATE 12 [hp_X]/1 mL; PHOSPHORUS 12 [hp_X]/1 mL; PULSATILLA PRATENSIS WHOLE 12 [hp_X]/1 mL; SILICON DIOXIDE 12 [hp_X]/1 mL
INACTIVE INGREDIENTS: WATER; ALCOHOL

DRUG FACTS:

ACTIVE INGREDIENTS:

(in each drop) Arsenicum Album 12X 9.98%, Carbo Vegetabilis 12X 9.98%, Causticum 12X 9.98%, Hydrastis Canadensis 6X 9.98%, Kali Carbonicum 12X 9.98%, Natrum Sulphuricum 12X 9.98%, Phosphorus 12X 9.98%, Pulsatilla 12X 9.98%, Silicea 12X 9.98%, Symphytum Officinale 6X 9.98%, Echinacea 3X 0.10%, Hypericum Perforatum 3X 0.10%.

PURPOSE:

Arsenicum Album - sneezing,** Carbo Vegetabilis -faintness,** Causticum – tightness in chest,** Hydrastis Canadensis – sinus congestion,** Kali Carbonicum – dry cough,** Natrum Sulphuricum – loose cough,** Phosphorus – eye irritation,** Pulsatilla – runny nose,** Silicea – shortness of breath,** Symphytum Officinale - headache,** Echinacea – watery eyes,** Hypericum Perforatum – hoarseness**

**Claims based on traditional homeopathic practice, not accepted medical evidence. Not FDA evaluated.

USES:

May temporarily relieve symptoms associated with exposure to pollutants, such as cough with expectoration.**

**Claims based on traditional homeopathic practice, not accepted medical evidence. Not FDA evaluated.

WARNINGS:

Stop use and ask a doctor if symptoms persist for more than 7 days.

If pregnant or breast-feeding, ask a health professional before use.

Keep out of reach of children. In case of overdose, get medical help or contact a Poison Control Center right away.

DO NOT USE IF TAMPER EVIDENT SEAL IS BROKEN OR MISSING

Store in a cool, dry place.

KEEP OUT OF REACH OF CHILDREN:

In case of overdose, get medical help or contact a Poison Control Center right away.

DIRECTIONS:

• Adults and children 5 to 10 drops orally, 3 times daily or as otherwise directed by a health care professional.

• Consult a physician for use in children under 12 years of age.

INACTIVE INGREDIENTS:

Demineralized water, 20% Ethanol.

QUESTIONS:

Dist. by Energique, Inc.

201 Apple Blvd.

Woodbine, IA 51579

800.869.8078

PACKAGE LABEL DISPLAY:

ENERGIQUE

SINCE 1987

HOMEOPATHIC REMEDY

SMOGSTAT

1 fl. oz. (30 ml)